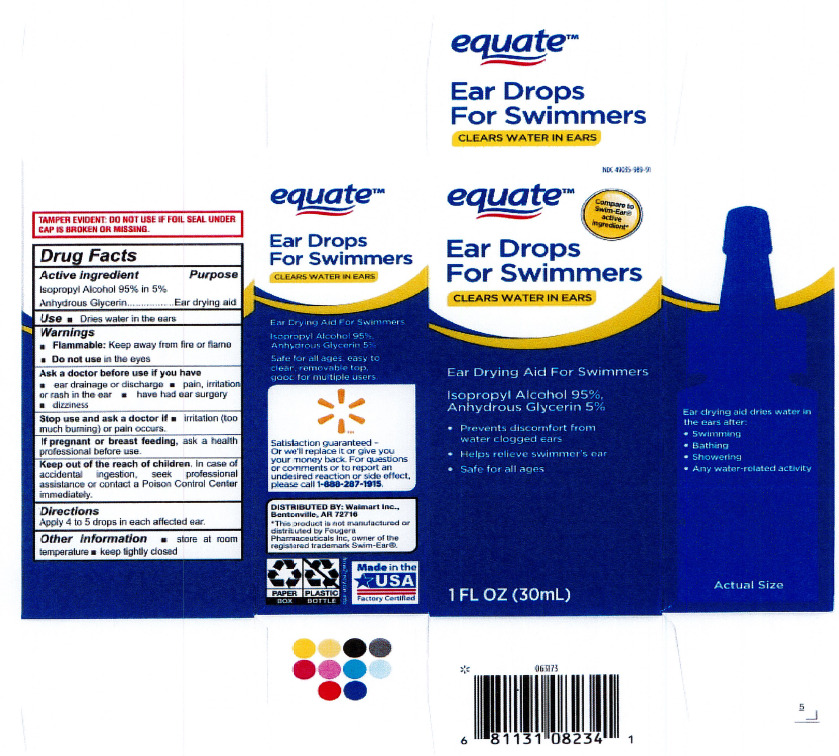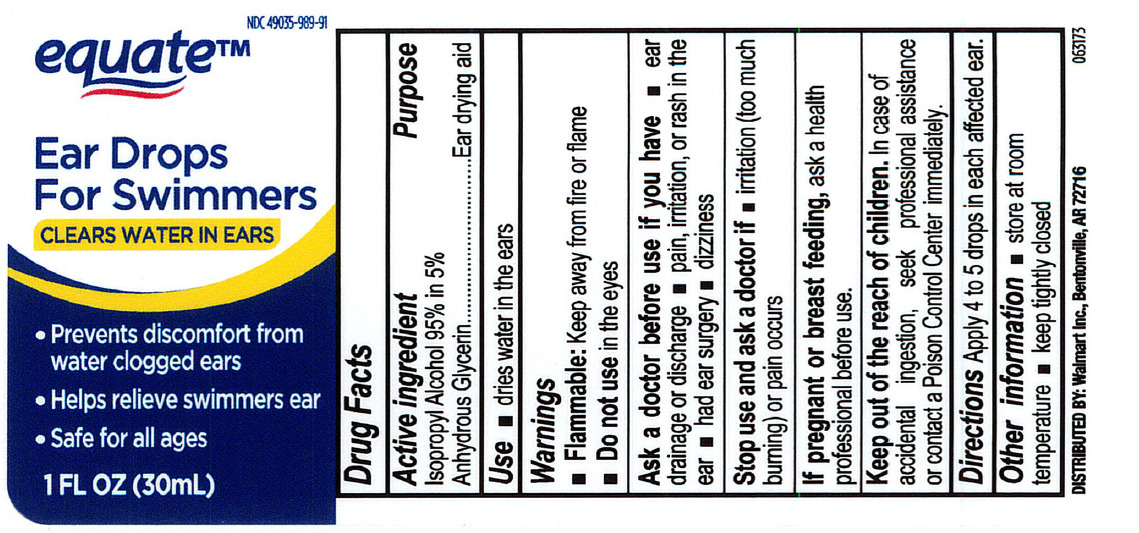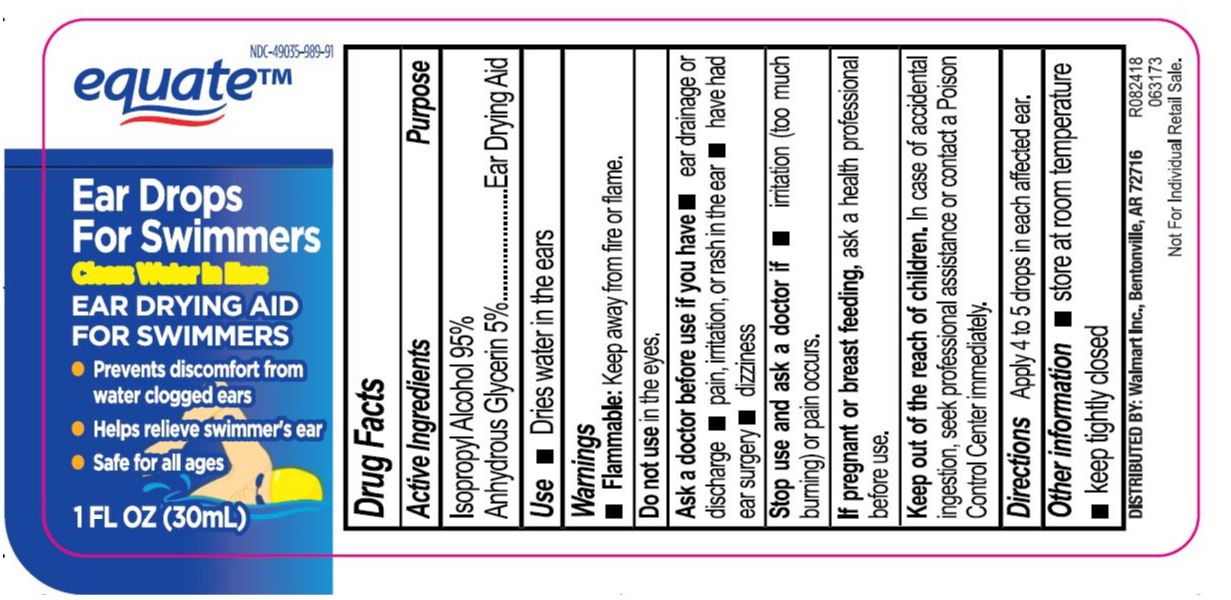 DRUG LABEL: Equate Swimmers Instant Ear Dry
NDC: 49035-989 | Form: LIQUID
Manufacturer: Walmart Stores, Inc
Category: otc | Type: HUMAN OTC DRUG LABEL
Date: 20231219

ACTIVE INGREDIENTS: ISOPROPYL ALCOHOL 950 mg/1 mL
INACTIVE INGREDIENTS: GLYCERIN 50 mg/1 mL

Equate Swimmers Instant Ear Dry

Drug Facts

Active Ingredient

Isopropyl Alcohol 95% in Anhydrous Glycerin

Purpose

Ear Drying Aid

Use

Dries water in the ears.

Warnings

Flammable: Keep away from fire and flame.

Do not use in the eyes

Directions

Apply 4 to 5 drops in each affected ear.

RECENT MAJOR CHANGES

Apply 4 to 5 drops in each affected ear. (12/2021)

Other Information

Store at room temperature.

Inactive Ingredient

Glycerin

Keep out of reach of children